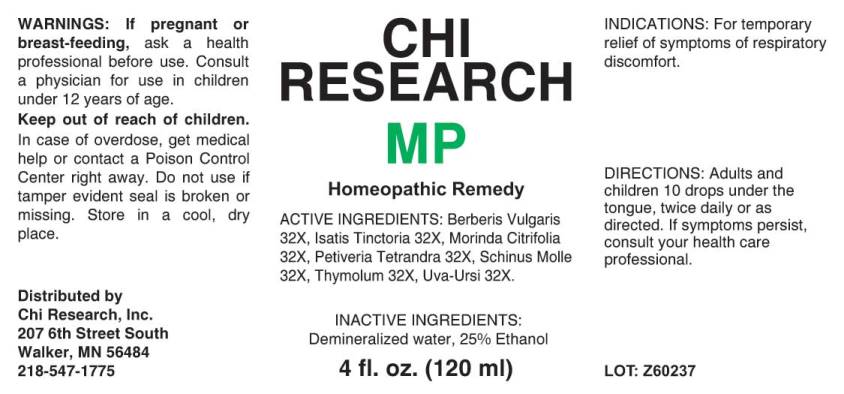 DRUG LABEL: MP
NDC: 52654-0007 | Form: LIQUID
Manufacturer: Chi Research, Inc.
Category: homeopathic | Type: HUMAN OTC DRUG LABEL
Date: 20200303

ACTIVE INGREDIENTS: BERBERIS VULGARIS ROOT BARK 32 [hp_X]/1 mL; ISATIS TINCTORIA WHOLE 32 [hp_X]/1 mL; NONI FRUIT JUICE 32 [hp_X]/1 mL; PETIVERIA ALLIACEA ROOT 32 [hp_X]/1 mL; SCHINUS MOLLE FRUITING TOP 32 [hp_X]/1 mL; THYMOL 32 [hp_X]/1 mL; ARCTOSTAPHYLOS UVA-URSI LEAF 32 [hp_X]/1 mL
INACTIVE INGREDIENTS: WATER; ALCOHOL

Drug Facts:

ACTIVE INGREDIENTS:

Berberis Vulgaris 32X, Isatis Tinctoria 32X, Morinda Citrifolia 32X, Petiveria Tetrandra 32X, Schinus Molle 32X, Thymolum 32X, Uva-Ursi 32X.

INDICATIONS:

For temporary relief of symptoms of respiratory discomfort.

WARNINGS:

If pregnant or breast-feeding, ask a health professional before use. Consult a physician for use in children under 12 years of age.

Keep out of reach of children. In case of overdose, get medical help or contact a Poison Control Center right away.

Do not use if tamper evident seal is broken or missing. Store in a cool, dry place.

Keep out of reach of children. In case of overdose, get medical help or contact a Poison Control Center right away.

DIRECTIONS:

Adults and children 10 drops under the tongue, twice daily or as directed. If symptoms persist, consult your health care professional.

INDICATIONS:

For temporary relief of symptoms of respiratory discomfort.

INACTIVE INGREDIENTS:

Demineralized water, 25% Ethanol

QUESTIONS:

Distributed by

Chi Research, Inc.

207 6th Street South

Walker, MN 56484

218-547-1775

PACKAGE LABEL DISPLAY:

CHI

RESEARCH

MP

Homeopathic Remedy

4 fl. oz. (120 ml)